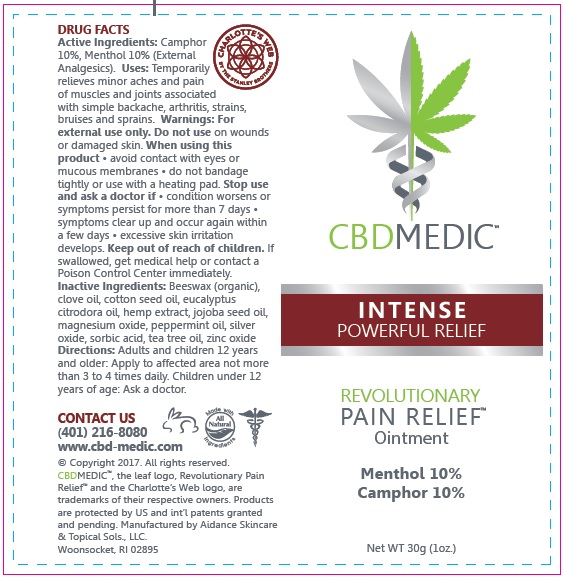 DRUG LABEL: CBD Medic - Intense Powerful Relief
NDC: 24909-723 | Form: OINTMENT
Manufacturer: Aidance Skincare & Topical Solutions, LLC
Category: otc | Type: HUMAN OTC DRUG LABEL
Date: 20170403

ACTIVE INGREDIENTS: CAMPHOR (SYNTHETIC) 10 g/100 g; MENTHOL 10 g/100 g
INACTIVE INGREDIENTS: CLOVE OIL; COTTONSEED OIL; EUCALYPTUS OIL; HEMP; JOJOBA OIL; MAGNESIUM OXIDE; PEPPERMINT OIL; SILVER OXIDE; SORBIC ACID; TEA TREE OIL; WHITE WAX; ZINC OXIDE

Drug Facts

Active Ingredients

Camphor 10%
Menthol 10%

Purpose

Camphor, Menthol - External Analgesics

Uses

Temporarily relieves minor aches and pain of muscles and joints associated with simple backache, arthritis, strains, bruises and sprains.

Warnings

For external use only. Do not use on wounds or damaged skin. When using this product - avoid contact with eyes or mucous membranes - do not bandage tightly or use with heating pad. Stop use and ask a doctor if - condition worsens or symptoms persist for more than 7 days - symptoms clear up and occur again within a few days - excessive skin irritation develops.

Keep out of reach of children.

If swallowed, get medical help or contact a Poison Control Center immediately.

Directions

Adults and children 12 years of age and older: Apply to affected area not more than 3 to 4 times daily. Children under 12 years of age: Ask a doctor.

Inactive Ingredients

Beeswax (organic), clove oil, cotton seed oil, eucalyptus citrodora oil, hemp extract, jojoba seed oil, magnesium oxide, peppermint oil, silver oxide, sorbic acid, tea tree oil, zinc oxide.

PRINCIPAL DISPLAY PANEL - 30g Size

CBDMEDIC

INTENSE
POWERFUL RELIEF
Revolutionary Pain Relief
Menthol 10%
Camphor 10%

Net WT 30g (1oz.)